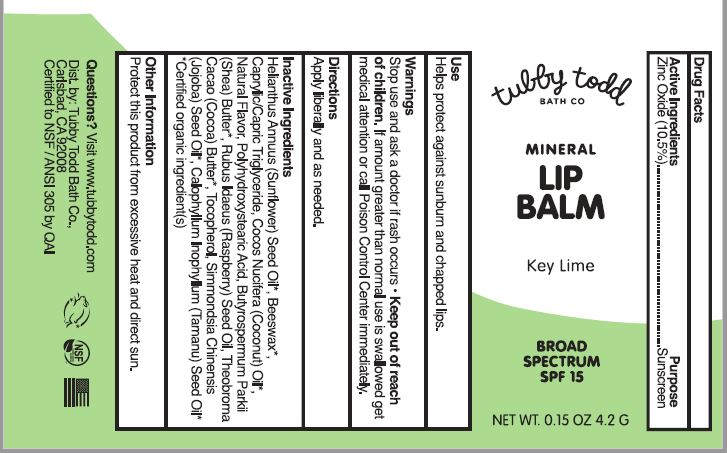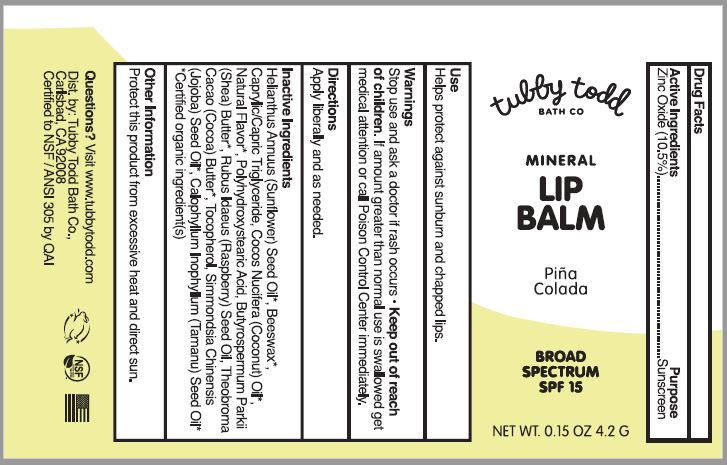 DRUG LABEL: Mineral Lip Balm
NDC: 73088-105 | Form: LIPSTICK
Manufacturer: TUBBY TODD
Category: otc | Type: HUMAN OTC DRUG LABEL
Date: 20241218

ACTIVE INGREDIENTS: ZINC OXIDE 10.5 g/100 g
INACTIVE INGREDIENTS: SUNFLOWER OIL; YELLOW WAX; MEDIUM-CHAIN TRIGLYCERIDES; COCONUT OIL; POLYHYDROXYSTEARIC ACID (2300 MW); SHEA BUTTER; RUBUS IDAEUS SEED; TOCOPHEROL; COCOA BUTTER; JOJOBA OIL; TAMANU OIL

Tubby Todd (as PLD) - Mineral Lip Balm SPF-15 (73088-105)

Active ingredients

Zinc Oxide 10.5%

Purpose

Sunscreen

Uses

Helps protect against sunburn and chapped lips.

Warnings

Stop use and ask a doctor if rash occurs

Keep out of reach of children.

If amount greater than normal use is swallowed get medical attention or call Poison Control Center immediately.

• Stop use and ask a doctor

if rash occurs

• Stop use and ask a doctor

if rash occurs

Directions

Apply liberally and as needed.

Other information

Protect this product from excessive heat and direct sun.

Inactive ingredients

Helianthus Annuus (Sunflower) Seed Oil*, Beeswax*, Caprylic/Capric Triglyceride, Cocos Nucifera (Coconut) Oil*, Natural Flavor*, Polyhydroxystearic Acid, Butyrospermum Parkii (Shea) Butter*, Rubus Idaeus (Raspberry) Seed Oil, Theobroma Cacao (Cocoa) Butter*, Tocopherol, Simmondsia Chinensis (Jojoba) Seed Oil*, Calophyllum Inophyllum (Tamanu) Seed Oil*
*Certified organic ingredient(s)